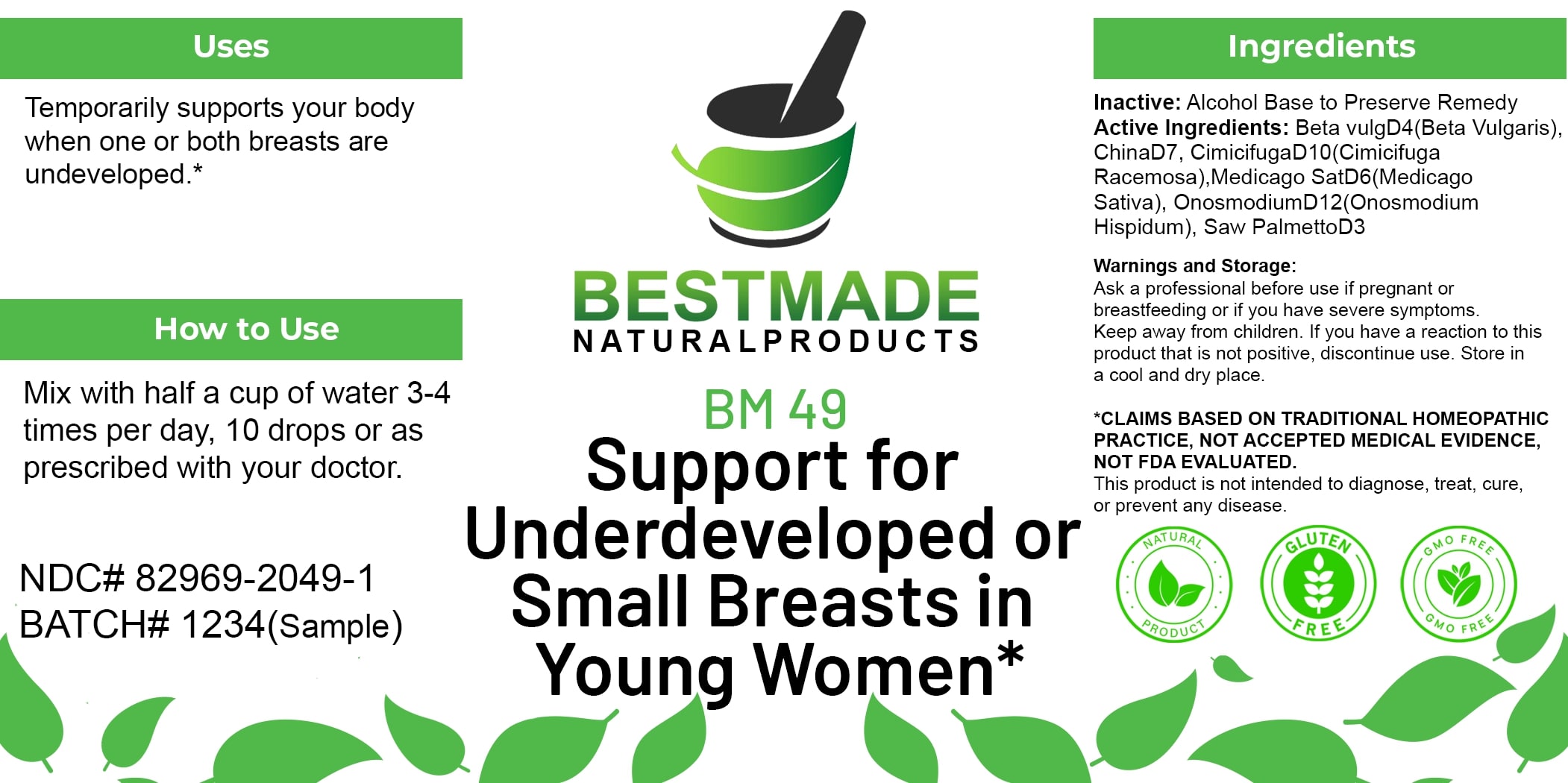 DRUG LABEL: Bestmade Natural Products BM49
NDC: 82969-2049 | Form: LIQUID
Manufacturer: Bestmade Natural Products
Category: homeopathic | Type: HUMAN OTC DRUG LABEL
Date: 20250218

ACTIVE INGREDIENTS: CINCHONA OFFICINALIS BARK 30 [hp_C]/30 [hp_C]; MEDICAGO SATIVA WHOLE 30 [hp_C]/30 [hp_C]; SAW PALMETTO 30 [hp_C]/30 [hp_C]; ONOSMODIUM VIRGINIANUM 30 [hp_C]/30 [hp_C]; BETA VULGARIS 30 [hp_C]/30 [hp_C]; CIMICIFUGA RACEMOSA ROOT 30 [hp_C]/30 [hp_C]
INACTIVE INGREDIENTS: ALCOHOL 30 [hp_C]/30 [hp_C]

BM49

DOSAGE AND ADMINISTRATION

How to Use

Mix with half a cup of water 3-4 times per day, 10 drops or as prescribed with your doctor.

INACTIVE INGREDIENT

Ingredients

Inactive: Alcohol Base to Preserve Remedy

ACTIVE INGREDIENT

Active Ingredients: Beta vulg D4 (Beta Vulgaris), China D7, Cimicifuga D10 (Cimicifuga Racemosa), Medicago Sat D6 (Medicago Sativa), Onosmodium D12 (Onosmodium Hispidum), Saw Palmetto D3

Uses

Temporarily supports your body when one or both breasts are undeveloped.*

*CLAIMS BASED ON TRADITIONAL HOMEOPATHIC PRACTICE, NOT ACCEPTED MEDICAL EVIDENCE, NOT FDA EVALUATED.

This product is not intended to diagnose, treat, cure, or prevent any disease.

Uses

Temporarily supports your body when one or both breasts are undeveloped.*

*CLAIMS BASED ON TRADITIONAL HOMEOPATHIC PRACTICE, NOT ACCEPTED MEDICAL EVIDENCE, NOT FDA EVALUATED.

This product is not intended to diagnose, treat, cure, or prevent any disease.

KEEP OUT OF REACH OF CHILDREN

Warnings and Storage:

Ask a professional before use if pregnant or breastfeeding or if you have severe symptoms. Keep away from children. If you have a reaction to this product that is not positive, discontinue use. Store in a cool and dry place.

Warnings and Storage:

Ask a professional before use if pregnant or breastfeeding or if you have severe symptoms. Keep away from children. If you have a reaction to this product that is not positive, discontinue use. Store in a cool and dry place.

*CLAIMS BASED ON TRADITIONAL HOMEOPATHIC PRACTICE, NOT ACCEPTED MEDICAL EVIDENCE, NOT FDA EVALUATED.

This product is not intended to diagnose, treat, cure, or prevent any disease.

Entire package label